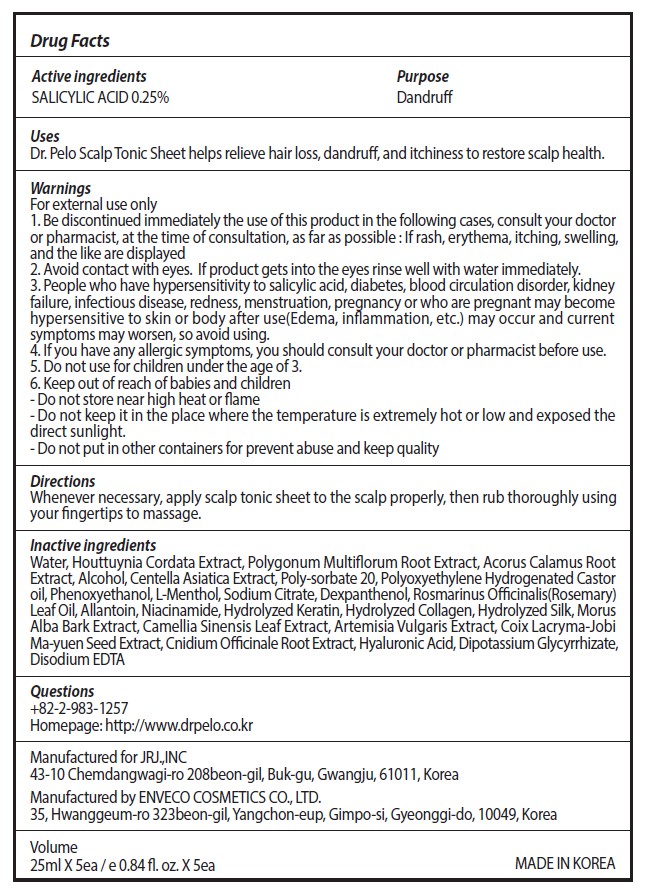 DRUG LABEL: Dr. Pelo Scalp Tonic Sheet
NDC: 81702-205 | Form: LIQUID
Manufacturer: JRJ.,INC
Category: otc | Type: HUMAN OTC DRUG LABEL
Date: 20210709

ACTIVE INGREDIENTS: SALICYLIC ACID 0.25 mg/100 mL
INACTIVE INGREDIENTS: CENTELLA ASIATICA WHOLE; LEVOMENTHOL; ROSEMARY OIL; GREEN TEA LEAF; COIX LACRYMA-JOBI VAR. MA-YUEN SEED; MORUS ALBA BARK; WATER; ACORUS CALAMUS ROOT; HOUTTUYNIA CORDATA FLOWERING TOP; REYNOUTRIA MULTIFLORA ROOT; ALCOHOL; POLYSORBATE 20; PEG-60 HYDROGENATED CASTOR OIL; PHENOXYETHANOL; SODIUM CITRATE, UNSPECIFIED FORM; DEXPANTHENOL; ALLANTOIN; NIACINAMIDE; ARTEMISIA VULGARIS ROOT; CNIDIUM OFFICINALE ROOT; HYALURONIC ACID; GLYCYRRHIZINATE DIPOTASSIUM; EDETATE DISODIUM ANHYDROUS

81702-205 Dr. Pelo Scalp Tonic Sheet

Active Ingredients

SALICYLIC ACID 0.25%

Purpose

Dandruff

Uses

Dr. Pelo Scalp Tonic Sheet helps relieve hair loss, dandruff, and itchiness to restore scalp health.

Warnings

For external use only

Stop use

1. Be discontinued immediately the use of this product in the following cases, consult your doctor or pharmacist, at the time of consultation, as far as possible : If rash, erythema, itching, swelling, and the like are displayed

2. Avoid contact with eyes. If product gets into the eyes rinse well with water immediately.

3. People who have hypersensitivity to salicylic acid, diabetes, blood circulation disorder, kidney failure, infectious disease, redness, menstruation, pregnancy or who are pregnant may become hypersensitive to skin or body after use(Edema, inflammation, etc.) may occur and current symptoms may worsen, so avoid using.

4. If you have any allergic symptoms, you should consult your doctor or pharmacist before use.

Do not use

5. Do not use for children under the age of 3.

Keep out of reach of children

6. Keep out of reach of babies and children

Directions

Whenever necessary, apply scalp tonic sheet to the scalp properly, then rub thoroughly using your fingertips to massage.

Inactive ingredients

Water, Houttuynia Cordata Extract, Polygonum Multiflorum Root Extract, Acorus Calamus Root
Extract, Alcohol, Centella Asiatica Extract, Poly-sorbate 20, Polyoxyethylene Hydrogenated Castor
oil, Phenoxyethanol, L-Menthol, Sodium Citrate, Dexpanthenol, Rosmarinus
Officinalis(Rosemary) Leaf Oil, Allantoin, Niacinamide, Hydrolyzed Keratin, Hydrolyzed Collagen,
Hydrolyzed Silk, Morus Alba Bark Extract, Camellia Sinensis Leaf Extract, Artemisia Vulgaris Extract,
Coix Lacryma-Jobi Ma-yuen Seed Extract, Cnidium Officinale Root Extract, Hyaluronic Acid,
Dipotassium Glycyrrhizate, Disodium EDTA

Other information

Do not store near high heat or flame

Do not keep it in the place where the temperature is extremely hor or low and exposed the direct sunlight.

Do not put in other containers for prevent abuse and keep quality